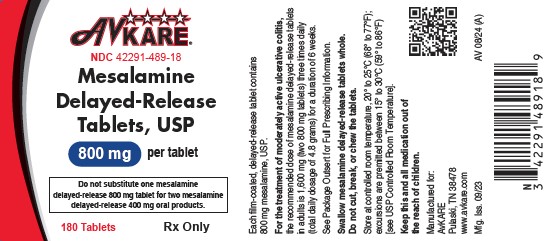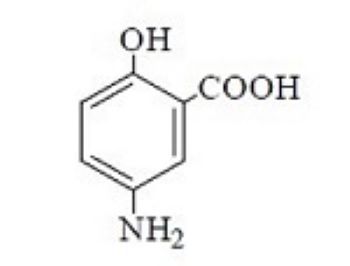 DRUG LABEL: Mesalamine
NDC: 42291-489 | Form: TABLET, DELAYED RELEASE
Manufacturer: AvKARE
Category: prescription | Type: HUMAN PRESCRIPTION DRUG LABEL
Date: 20260114

ACTIVE INGREDIENTS: MESALAMINE 800 mg/1 1
INACTIVE INGREDIENTS: SILICON DIOXIDE; DIBUTYL SEBACATE; FD&C RED NO. 40; FD&C YELLOW NO. 6 ALUMINUM LAKE; FERRIC OXIDE RED; LACTOSE MONOHYDRATE; MAGNESIUM STEARATE; METHACRYLIC ACID - METHYL METHACRYLATE COPOLYMER (1:1); METHACRYLIC ACID - METHYL METHACRYLATE COPOLYMER (1:2); POLYETHYLENE GLYCOL 3350; POLYETHYLENE GLYCOL 6000; POLYVINYL ALCOHOL, UNSPECIFIED; POVIDONE K30; SODIUM STARCH GLYCOLATE TYPE A; TALC; TITANIUM DIOXIDE; ISOPROPYL ALCOHOL; BUTYL ALCOHOL; PROPYLENE GLYCOL; SHELLAC

HIGHLIGHTS OF PRESCRIBING INFORMATION

Mesalamine Delayed-Release Tablets, USP
Rx only
These highlights do not include all the information needed to use MESALAMINE DELAYED-RELEASE TABLETS safely and effectively. See full prescribing information for MESALAMINE DELAYED-RELEASE TABLETS.
Initial U.S. Approval: 1987

1 INDICATIONS AND USAGE

Mesalamine delayed-release tablets are an aminosalicylate indicated for the treatment of moderately active ulcerative colitis in adults. (1)

Limitation of Use:

Safety and effectiveness of mesalamine delayed-release tablets beyond 6 weeks have not been established (1)

2 DOSAGE AND ADMINISTRATION

Important Administration Instructions:

- Do not substitute one mesalamine delayed-release 800 mg tablet for two mesalamine delayed-release 400 mg oral products. (2.1)
- Evaluate renal function prior to initiation of mesalamine delayed-release tablets. (2.1, 5.1)
- Take on an empty stomach, at least 1 hour before and 2 hours after a meal. (2.1)
- Swallow whole; do not cut, break or chew the tablets. (2.1)
- Drink an adequate amount of fluids. (2.1, 5.7)

Treatment of Moderately Active Ulcerative Colitis:

- Recommended dosage is 1,600 mg (two 800 mg tablets) three times daily for 6 weeks. (2.2)

3 DOSAGE FORMS AND STRENGTHS

Delayed-release tablets: 800 mg (3)

4 CONTRAINDICATIONS

Known or suspected hypersensitivity to salicylates or aminosalicylates or to any of the ingredients of mesalamine delayed-release tablets. (4, 5.3)

5 WARNINGS AND PRECAUTIONS

- Renal Impairment: Assess renal function at the beginning of treatment and periodically during treatment. Evaluate the risks and benefits in patients with known renal impairment or taking nephrotoxic drugs; monitor renal function. Discontinue mesalamine delayed-release if renal function deteriorates. (5.1, 7.1, 8.6)
- Mesalamine-induced Acute Intolerance Syndrome: Symptoms may be difficult to distinguish from an ulcerative colitis exacerbation; monitor for worsening symptoms; discontinue if acute intolerance syndrome suspected. (5.2)
- Hypersensitivity Reactions, including Myocarditis and Pericarditis: Evaluate patients immediately and discontinue if a hypersensitivity reaction is suspected. (5.3)
- Hepatic Failure: Evaluate the risks and benefits in patients with known liver impairment. (5.4)
- Severe Cutaneous Adverse Reactions: Discontinue at the first signs or symptoms of severe cutaneous adverse reactions or other signs of hypersensitivity and consider further evaluation. (5.5)
- Photosensitivity: Advise patients with pre-existing skin conditions to avoid sun exposure, wear protective clothing, and use a broad-spectrum sunscreen when outdoors. (5.6)
- Nephrolithiasis:Mesalamine-containing stones are undetectable by standard radiography or computed tomography (CT). Ensure adequate hydration during treatment. (5.7)
- Iron Content of Mesalamine Delayed-Release Tablets: Consider the iron content of mesalamine delayed-release tablets in patients taking iron supplementation and those at risk of iron overload. (5.8)
- Interference with Laboratory Tests: Use of mesalamine may lead to spuriously elevated test results when measuring urinary normetanephrine by liquid chromatography with electrochemical detection. (5.9)

6 ADVERSE REACTIONS

The most common adverse reactions (≥2%) are headache, nausea, nasopharyngitis, abdominal pain, and worsening of ulcerative colitis (6.1)

To report SUSPECTED ADVERSE REACTIONS, contact AvKARE at 1-855-361-3993 or FDA at 1-800-FDA-1088 or www.fda.gov/medwatch.

7 DRUG INTERACTIONS

- Nephrotoxic Agents including NSAIDs: Increased risk of nephrotoxicity; monitor for changes in renal function and mesalaminerelated adverse reactions. (7.1)
- Azathioprine or 6-Mercaptopurine: Increased risk of blood disorders; monitor complete blood cell counts and platelet counts. (7.2)

8 USE IN SPECIFIC POPULATIONS

Geriatric Patients: Increased risk of blood dyscrasias; monitor complete blood cell counts and platelet counts. (8.5)

FULL PRESCRIBING INFORMATION

1 INDICATIONS AND USAGE

Mesalamine delayed-release tablets are indicated for the treatment of moderately active ulcerative colitis in adults.

Limitations of Use:

Safety and effectiveness of mesalamine delayed-release tablets beyond 6 weeks have not been established.

2 DOSAGE AND ADMINISTRATION

2.1 Important Administration Instructions

- Do not substitute one mesalamine delayed-release 800 mg tablet for two mesalamine delayed-release 400 mg oral products [see Clinical Pharmacology (12.3)] .
- Evaluate renal function prior to initiation of mesalamine delayed-release tablets.
- Take mesalamine delayed-release tablets on an empty stomach, at least 1 hour before and 2 hours after a meal [see Clinical Pharmacology (12.3)] .
- Swallow mesalamine delayed-release tablets whole. Do not cut, break or chew the tablets.
- Drink an adequate amount of fluids [see Warnings and Precautions (5.7)] .
- Intact, partially intact, and/or tablet shells have been reported in the stool; Instruct patients to contact their healthcare provider if this occurs repeatedly.
- Protect mesalamine delayed-release tablets from moisture.

2.2 Dosage Information

For the treatment of moderately active ulcerative colitis, the recommended dosage of mesalamine delayed-release tablets in adults is 1,600 mg (two 800 mg tablets) three times daily (total daily dosage of 4.8 grams) for a duration of 6 weeks.

3 DOSAGE FORMS AND STRENGTHS

Mesalamine delayed-release tablets, USP: 800 mg (reddish brown, film-coated, modified capsule-shaped tablets containing 800 mg mesalamine, USP and imprinted with “TV M80” in white ink on one side and plain on the other side).

4 CONTRAINDICATIONS

Mesalamine delayed-release tablets are contraindicated in patients with known or suspected hypersensitivity to salicylates or aminosalicylates or to any of the ingredients of mesalamine delayed-release tablets [see Warnings and Precautions (5.3), Adverse Reactions (6.2), and Description (11)] .

5 WARNINGS AND PRECAUTIONS

5.1 Renal Impairment

Renal impairment, including minimal change disease, acute and chronic interstitial nephritis, and, rarely, renal failure, has been reported in patients taking products such as mesalamine delayed-release tablets that contain or are converted to mesalamine [see Adverse Reactions (6.2)] . In animal studies, the kidney was the principal organ of mesalamine toxicity [see Adverse Reactions (6.2), Nonclinical Toxicology (13.2)] .

Evaluate renal function prior to initiation of mesalamine delayed-release and periodically while on therapy.

Evaluate the risks and benefits of using mesalamine delayed-release in patients with known renal impairment or history of renal disease or taking concomitant nephrotoxic drugs. Discontinue mesalamine delayed-release if renal function deteriorates while on therapy [see Drug Interactions (7.1), Use in Specific Populations (8.6)] .

5.2 Mesalamine-Induced Acute Intolerance Syndrome

Mesalamine has been associated with an acute intolerance syndrome that may be difficult to distinguish from an exacerbation of ulcerative colitis. Exacerbation of the symptoms of colitis has been reported in 2.3% of mesalamine delayed-release-treated patients in controlled clinical trials. This acute reaction, characterized by cramping, abdominal pain, bloody diarrhea, and occasionally by fever, headache, malaise, pruritus, rash, and conjunctivitis, has been reported after the initiation of mesalamine delayed-release tablets as well as other mesalamine products. Symptoms usually abate when mesalamine delayed-release tablets are discontinued. Monitor patients for worsening of these symptoms while on treatment. If acute intolerance syndrome is suspected, promptly discontinue treatment with mesalamine delayed-release.

5.3 Hypersensitivity Reactions

Hypersensitivity reactions have been reported in patients taking sulfasalazine. Some patients may have a similar reaction to mesalamine delayed-release tablets or to other compounds that contain or are converted to mesalamine.

As with sulfasalazine, mesalamine-induced hypersensitivity reactions may present as internal organ involvement, including myocarditis, pericarditis, nephritis, hepatitis, pneumonitis, and hematologic abnormalities. Evaluate patients immediately if signs or symptoms of a hypersensitivity reaction are present. Discontinue mesalamine delayed-release tablets if an alternative etiology for the signs or symptoms cannot be established.

5.4 Hepatic Failure

There have been reports of hepatic failure in patients with pre-existing liver disease who have been administered mesalamine. Evaluate the risks and benefits of using mesalamine delayed-release in patients with known liver impairment.

5.5 Severe Cutaneous Adverse Reactions

Severe cutaneous adverse reactions including Stevens-Johnson syndrome (SJS) and toxic epidermal necrolysis (TEN), drug reaction with eosinophilia and systemic symptoms (DRESS), and acute generalized exanthematous pustulosis (AGEP) have been reported with use of mesalamine [see Adverse Reactions (6.2)] . Discontinue mesalamine delayed-release tablets at the first appearance of signs or symptoms of severe cutaneous adverse reactions, or other signs of hypersensitivity and consider further evaluation.

5.6 Photosensitivity

Patients treated with mesalamine or sulfasalazine who have pre-existing skin conditions such as atopic dermatitis and atopic eczema have reported more severe photosensitivity reactions. Advise patients to avoid sun exposure, wear protective clothing, and use a broad-spectrum sunscreen when outdoors.

5.7 Nephrolithiasis

Cases of nephrolithiasis have been reported with the use of mesalamine, including stones of 100% mesalamine content. Mesalamine-containing stones are radiotransparent and undetectable by standard radiography or computed tomography (CT). Ensure adequate fluid intake during treatment with mesalamine delayed-release.

5.8 Iron Content of Mesalamine Delayed-Release Tablets

Mesalamine delayed-release tablets contains iron oxide as a colorant in the coating of the delayed-release tablets. Each 800 mg delayed-release tablet contains 0.5001 mg of iron. The total content of iron is 3.0006 mg at the recommended daily dosage [see Dosage and Administration (2.2)] . Before prescribing mesalamine delayed-release to patients receiving iron supplementation or those at risk for developing iron overload, consider the combined daily amount of iron from all sources, including mesalamine delayed-release.

5.9 Interference with Laboratory Tests

Use of mesalamine delayed-release may lead to spuriously elevated test results when measuring urinary normetanephrine by liquid chromatography with electrochemical detection because of the similarity in the chromatograms of normetanephrine and the main metabolite of mesalamine, N-acetyl-5-aminosalicylic acid (N-Ac-5-ASA). Consider an alternative, selective assay for normetanephrine.

6 ADVERSE REACTIONS

The following serious or clinically significant adverse described elsewhere in labeling are:

- Renal Impairment [see Warnings and Precautions (5.1)]
- Mesalamine-Induced Acute Intolerance Syndrome [see Warnings and Precautions (5.2)]
- Hypersensitivity Reactions [see Warnings and Precautions (5.3)]
- Hepatic Failure [see Warnings and Precautions (5.4)]
- Severe Cutaneous Adverse Reactions [see Warnings and Precautions (5.5)]
- Photosensitivity [see Warnings and Precautions (5.6)]
- Nephrolithiasis [see Warnings and Precautions (5.7)]

6.1 Clinical Trials Experience

Because clinical trials are conducted under widely varying conditions, adverse reaction rates observed in the clinical trials of a drug cannot be directly compared to rates in the clinical trials of another drug and may not reflect the rates observed in practice.

Mesalamine delayed-release has been evaluated in 896 patients with ulcerative colitis in controlled studies. Three six-week, active-controlled studies were conducted comparing mesalamine delayed-release 4.8 grams per day with mesalamine-delayed release tablets 2.4 grams per day in patients with mildly to moderately active ulcerative colitis. In these studies, 727 patients were dosed with mesalamine delayed-release (800 mg) tablets and 732 patients were dosed with mesalamine delayed-release (400 mg) tablets.

The most common reactions reported in the mesalamine delayed-release group were headache (4.7%), nausea (2.8%), nasopharyngitis (2.5%), abdominal pain (2.3%), diarrhea (1.7%), and dyspepsia (1.7%); Table 1 enumerates adverse reactions that occurred in the three studies. The most common reactions in patients with moderately active ulcerative colitis (602 patients dosed with mesalamine delayed-release and 618 patients dosed with mesalamine delayed-release 400 mg) were the same as all treated patients.

Discontinuations due to adverse reactions occurred in 3.9% of patients in the mesalamine delayed-release group and in 4.2% of patients in the mesalamine delayed-release tablet comparator group. The most common cause for discontinuation was gastrointestinal symptoms associated with ulcerative colitis.

Serious adverse reactions occurred in 0.8% of patients in the mesalamine delayed-release group and in 1.8% of patients in the mesalamine delayed-release tablet comparator group. The majority involved the gastrointestinal system.

Table 1. Adverse Reactions Occurring in ≥1% of All Treated Patients (Three studies combined)
Adverse Reaction | Mesalamine delayed-release 2.4 grams per day (400 mg Tablet) (N = 732) | Mesalamine delayed-release 4.8 grams per day (800 mg Tablet) (N = 727)
Headache | 4.9 % | 4.7 %
Nausea | 2.9 % | 2.8 %
Nasopharyngitis | 1.4 % | 2.5 %
Abdominal pain | 2.3 % | 2.3 %
Diarrhea | 1.9 % | 1.7 %
Dyspepsia | 0.8 % | 1.7 %
Vomiting | 1.6 % | 1.4 %
Flatulence | 0.7 % | 1.2 %
Influenza | 1.2 % | 1.0 %
Pyrexia | 1.2 % | 0.7 %
Cough | 1.4 % | 0.3 %
N = number of patients within specified treatment group Percent = percentage of patients in category and treatment group

6.2 Postmarketing Experience

The following adverse reactions have been identified during post-approval use of mesalamine delayed-release or other mesalamine-containing products or products that are metabolized to mesalamine. Because these reactions are reported voluntarily from a population of uncertain size, it is not always possible to reliably estimate their frequency or establish a causal relationship to drug exposure.

Body as a Whole: Facial edema, edema, peripheral edema, asthenia, chills, infection, malaise, pain, neck pain, chest pain, back pain, abdominal enlargement, lupus-like syndrome, drug fever (rare).

Cardiovascular: Pericarditis (rare) and myocarditis (rare) [see Warnings and Precautions (5.3)] , pericardial effusion, vasodilation, migraine.

Endocrine: Nephrogenic diabetes insipidus.

Gastrointestinal: Dry mouth, stomatitis, oral ulcers, anorexia, increased appetite, eructation, pancreatitis, cholecystitis, gastritis, gastroenteritis, gastrointestinal bleeding, perforated peptic ulcer (rare), constipation, hemorrhoids, rectal hemorrhage, bloody diarrhea, tenesmus, stool abnormality.

Hepatic: There have been rare reports of hepatotoxicity, including jaundice, cholestatic jaundice, hepatitis, and possible hepatocellular damage including liver necrosis and liver failure. Some of these cases were fatal. Asymptomatic elevations of liver enzymes which usually resolve during continued use or with discontinuation of the drug have also been reported. One case of Kawasaki-like syndrome, that included changes in liver enzymes, was also reported [see Warnings and Precautions (5.4)] .

Hematologic: Agranulocytosis (rare), aplastic anemia (rare), anemia, thrombocytopenia, leukopenia, eosinophilia, lymphadenopathy.

Musculoskeletal: Gout, rheumatoid arthritis, arthritis, arthralgia, joint disorder, myalgia, hypertonia.

Neurological/Psychiatric: Anxiety, depression, somnolence, insomnia, nervousness, confusion, emotional lability, dizziness, vertigo, tremor, paresthesia, hyperesthesia, peripheral neuropathy (rare), Guillain-Barré syndrome (rare), transverse myelitis (rare), and intracranial hypertension.

Respiratory/Pulmonary: Sinusitis, rhinitis, pharyngitis, asthma exacerbation, pleuritis/pleurisy, bronchitis, eosinophilic pneumonia, interstitial pneumonitis.

Skin: Alopecia, psoriasis (rare), pyoderma gangrenosum (rare), erythema nodosum, acne, dry skin, sweating, pruritus, urticaria, rash, SJS/TEN, DRESS, and AGEP [see Warnings and Precautions (5.5)] .

Special Senses: Ear pain, tinnitus, ear congestion, ear disorder, conjunctivitis, eye pain, blurred vision, vision abnormality, taste perversion.

Renal/Urogenital: Renal failure (rare), interstitial nephritis, minimal change disease, nephrolithiasis [see Warnings and Precautions (5.1, 5.7)] , dysuria, urinary frequency and urgency, hematuria, epididymitis, decreased libido, dysmenorrhea, menorrhagia. Urine discoloration occurring ex-vivo caused by contact of mesalamine, including inactive metabolite, with surfaces or water treated with hypochlorite containing bleach.

Laboratory Abnormalities: Elevated AST (SGOT) or ALT (SGPT), elevated alkaline phosphatase, elevated GGT, elevated LDH, elevated bilirubin, elevated serum creatinine and BUN.

To report SUSPECTED ADVERSE REACTIONS, contact AvKARE at 1-855-361-3993 or FDA at 1-800-FDA-1088 or www.fda.gov/medwatch.

7 DRUG INTERACTIONS

7.1 Nephrotoxic Agents, Including Non-Steroidal Anti-Inflammatory Drugs

The concurrent use of mesalamine with known nephrotoxic agents, including nonsteroidal anti-inflammatory drugs (NSAIDs) may increase the risk of nephrotoxicity. Monitor patients taking nephrotoxic drugs for changes in renal function and mesalamine-related adverse reactions [see Warnings and Precautions (5.1)] .

7.2 Azathioprine or 6-Mercaptopurine

The concurrent use of mesalamine with azathioprine or 6-mercaptopurine and/or other drugs known to cause myelotoxicity may increase the risk for blood disorders, bone marrow failure, and associated complications. If concomitant use of mesalamine delayed-release and azathioprine or 6-mercaptopurine cannot be avoided, monitor blood tests, including complete blood cell counts and platelet counts.

7.3 Interference with Urinary Normetanephrine Measurements

Use of mesalamine delayed-release may lead to spuriously elevated test results when measuring urinary normetanephrine by liquid chromatography with electrochemical detection [see Warnings and Precautions (5.9)] . Consider an alternative, selective assay for normetanephrine.

8 USE IN SPECIFIC POPULATIONS

8.1 Pregnancy

Risk Summary

Limited published data on mesalamine use in pregnant women are insufficient to inform a drug-associated risk. No fetal harm was observed in animal reproduction studies of mesalamine in rats and rabbits at oral doses approximately 0.97 times (rat) and 1.95 times (rabbit) the recommended human dose (see Data).

The estimated background risk of major birth defects and miscarriage for the indicated populations is unknown. In the U.S. general population, the estimated background risk of major birth defects and miscarriage in clinically recognized pregnancies is 2% to 4% and 15% to 20%, respectively.

Data

Animal Data

Reproduction studies with mesalamine were performed during organogenesis in rats and rabbits at oral doses up to 480 mg/kg/day. There was no evidence of harm to the fetus. These mesalamine doses were about 0.97 times (rat) and 1.95 times (rabbit) the recommended human dose of 4.8 grams per day, based on body surface area.

8.2 Lactation

Risk Summary

Mesalamine and its N-acetyl metabolite are present in human milk in undetectable to small amounts (see Data).

There are limited reports of diarrhea in breastfed infants. There is no information on the effects of the drug on milk production. The developmental and health benefits of breastfeeding should be considered along with the mother’s clinical need for mesalamine delayed-release and any potential adverse effects on the breastfed infant from the drug or from the underlying maternal condition.

Clinical Considerations

Monitor breastfed infants for diarrhea.

Data

Human Data

In published lactation studies, maternal mesalamine doses from various oral and rectal formulations and products ranged from 500 mg to 3 g daily. The concentration of mesalamine in milk ranged from non-detectable to 0.11 mg/L. The concentration of the N-acetyl-5-aminosalicylic acid metabolite ranged from 5 mg/L to 18.1 mg/L. Based on these concentrations, estimated infant daily dosages for an exclusively breastfed infant are 0 to 0.017 mg/kg/day of mesalamine and 0.75 mg/kg/day to 2.72 mg/kg/day of N-acetyl-5-aminosalicylic acid.

8.4 Pediatric Use

Safety and effectiveness of mesalamine delayed-release in pediatric patients have not been established. See the prescribing information for other approved mesalamine products for the safety and effectiveness of these products in pediatric patients.

8.5 Geriatric Use

Clinical studies of mesalamine delayed-release did not include sufficient numbers of patients aged 65 years and over to determine whether they respond differently than younger patients. Reports from uncontrolled clinical studies and postmarketing reporting systems suggested a higher incidence of blood dyscrasias (i.e., agranulocytosis, neutropenia, and pancytopenia) in patients who were 65 years or older compared to younger patients taking mesalaminecontaining products such as mesalamine delayed-release. Monitor complete blood cell counts and platelet counts in elderly patients during therapy with mesalamine delayed-release.

In general, consider the greater frequency of decreased hepatic, renal, or cardiac function, and of concomitant disease or other drug therapy in elderly patients when prescribing mesalamine delayed-release [see Use in Specific Populations (8.6)] .

8.6 Renal Impairment

Mesalamine is known to be substantially excreted by the kidney, and the risk of adverse reactions may be greater in patients with impaired renal function. Evaluate renal function in all patients prior to initiation and periodically while on mesalamine delayed-release therapy. Monitor patients with known renal impairment or history of renal disease or taking nephrotoxic drugs for decreased renal function and mesalamine-related adverse reactions. Discontinue mesalamine delayed-release if renal function deteriorates while on therapy [see Warnings and Precautions (5.1), Adverse Reactions (6.2), Drug Interactions (7.1)] .

10 OVERDOSAGE

Mesalamine delayed-release is an aminosalicylate, and symptoms of salicylate toxicity include nausea, vomiting and abdominal pain, tachypnea, hyperpnea, tinnitus, and neurologic symptoms (headache, dizziness, confusion, seizures). Severe salicylate intoxication may lead to electrolyte and blood pH imbalance and potentially to other organ (e.g., renal and liver) involvement. There is no specific antidote for mesalamine overdose; however, conventional therapy for salicylate toxicity may be beneficial in the event of acute overdosage and may include gastrointestinal tract decontamination to prevent of further absorption. Correct fluid and electrolyte imbalance by the administration of appropriate intravenous therapy and maintain adequate renal function.

Mesalamine delayed-release is a pH dependent delayed-release product and this factor should be considered when treating a suspected overdose.

11 DESCRIPTION

Each mesalamine delayed-release tablet, USP for oral administration contains 800 mg of mesalamine, USP, an aminosalicylate. Mesalamine delayed-release tablets, USP have an outer protective coat consisting of a combination of acrylic based resins, methacrylic acid and methyl methacrylate copolymer (1:2) and methacrylic acid and methyl methacrylate copolymer (1:1). The inner coat consists of an acrylic based resin, methacrylic acid and methyl methacrylate copolymer (1:2), which dissolves at pH 7 or greater, releasing mesalamine in the terminal ileum and beyond for topical anti-inflammatory action in the colon. Mesalamine, USP (also referred to as 5-aminosalicylic acid or 5-ASA) has the chemical name 5-amino-2-hydroxybenzoic acid; its structural formula is:

Molecular Weight: 153.1

Molecular Formula: C7H7NO3

Inactive Ingredients:Each tablet contains colloidal silicon dioxide, dibutyl sebacate, FD&C Red #40/Allura Red AC Aluminum Lake, FD&C Yellow #6/Sunset Yellow FCF Aluminum Lake, iron oxide red, lactose monohydrate, magnesium stearate, methacrylic acid and methyl methacrylate copolymer (1:1), methacrylic acid and methyl methacrylate copolymer (1:2), polyethylene glycol 3350, polyethylene glycol 6000, polyvinyl alcohol, povidone K-30, sodium starch glycolate (type A), talc, and titanium dioxide. In addition the imprinting white ink contains isopropyl alcohol, n-butyl alcohol, propylene glycol, and shellac glaze.

12 CLINICAL PHARMACOLOGY

12.1 Mechanism of Action

The mechanism of action of mesalamine is not fully understood, but appears to be a topical anti-inflammatory effect on colonic epithelial cells. Mucosal production of arachidonic acid metabolites, both through the cyclooxygenase pathways, that is, prostanoids, and through the lipoxygenase pathways, that is, leukotrienes and hydroxyeicosatetraenoic acids, is increased in patients with ulcerative colitis, and it is possible that mesalamine diminishes inflammation by blocking cyclooxygenase and inhibiting prostaglandin production in the colon.

12.3 Pharmacokinetics

Absorption

Plasma concentrations of mesalamine (5-aminosalicylic acid; 5-ASA) and its metabolite, N-acetyl-5-aminosalicylic acid (N-Ac-5-ASA) are highly variable following administration of mesalamine delayed-release tablets. Following single dose oral administration of mesalamine delayed-release 800 mg tablet in healthy subjects (N = 139) under fasted conditions, the mean Cmax, AUC8-48hand AUC0-tldcvalues were 208 ng/mL, 2296 ng.h/mL, and 2533 ng.h/mL, respectively. The median [range] Tmaxfor mesalamine following administration of mesalamine delayed-release 800 mg tablet was approximately 24 hours [4 to 72 hours], reflecting the delayed-release characteristics of the formulation.

Based on cumulative urinary recovery of mesalamine and N-Ac-5-ASA from single dose studies in healthy subjects, approximately 20% of the orally administered mesalamine in mesalamine delayed-release tablets is systemically absorbed.

Food Effect:A high calorie (800 to 1,000 calories), high fat (approximately 50 % of total caloric content) meal increased mesalamine Cmaxby 2.4-fold and mesalamine systemic exposure (AUC8-48and AUC0-tldc) by 2.8-fold; the median lag-time increased by 8 hours and median tmaxby 6 hours (from 24 to 30 hours) [see Dosage and Administration (2.1)] .

Comparative exposure between one mesalamine delayed-release 800 mg tablet and two mesalamine delayed-release 400 mg oral products is unknown [see Dosage and Administration (2.1)] .

Elimination

Metabolism

The absorbed mesalamine is acetylated in the gut mucosal wall and by the liver to N-Ac-5ASA.

Excretion

Absorbed mesalamine is excreted mainly by the kidneys as N-acetyl-5-aminosalicylic acid. Unabsorbed mesalamine is excreted in feces.

13 NONCLINICAL TOXICOLOGY

13.1 Carcinogenesis, Mutagenesis, Impairment of Fertility

Dietary mesalamine was not carcinogenic in rats at doses as high as 480 mg/kg/day, or in mice at 2,000 mg/kg/day. These doses are approximately 0.97 and 2.0 times the 4.8 grams per day mesalamine delayed-release dose (based on body surface area). Mesalamine was not genotoxic in the Ames test, the Chinese hamster ovary cell chromosomal aberration assay, and the mouse micronucleus test. Mesalamine, at oral doses up to 480 mg/kg/day (about 0.97 times the recommended human treatment dose based on body surface area), was found to have no effect on fertility or reproductive performance of male and female rats.

13.2 Animal Toxicology and/or Pharmacology

In animal studies (rats, mice, dogs), the kidney was the principal organ for toxicity. (In the following, comparisons of animal dosing to recommended human dosing are based on body surface area and a 4.8 grams per day dose for a 60 kg person.)

Mesalamine causes renal papillary necrosis in rats at single doses of approximately 750 mg/kg to 1,000 mg/kg (1.5 to 2.0 times the recommended human dose). Doses of 170 and 360 mg/kg/day (about 0.3 and 0.73 times the recommended human dose) given to rats for six months produced papillary necrosis, papillary edema, tubular degeneration, tubular mineralization, and urothelial hyperplasia.

In mice, oral doses of 4,000 mg/kg/day (approximately 4.1 times the recommended human dose) for three months produced tubular nephrosis, multifocal/diffuse tubulo-interstitial inflammation, and multifocal/diffuse papillary necrosis.

In dogs, single doses of 6,000 mg (approximately 6.25 times the recommended human dose) of delayed-release mesalamine tablets resulted in renal papillary necrosis but were not fatal. Renal changes have occurred in dogs given chronic administration of mesalamine at doses of 80 mg/kg/day (0.5 times the recommended human dose).

14 CLINICAL STUDIES

The efficacy of mesalamine delayed-release at 4.8 grams per day was studied in a six-week, randomized, double-blind, active-controlled study in 772 patients with moderately active ulcerative colitis (UC). Moderately active UC was defined as a Physician’s Global Assessment (PGA) score of 2; the PGA is a four-point scale (0 to 3) that encompasses the clinical assessments of rectal bleeding, stool frequency, and sigmoidoscopy findings.

Patients were randomized 1:1 to the mesalamine delayed-release 4.8 grams per day group (two mesalamine delayed-release tablets three times a day) or the mesalamine delayed-release 2.4 grams per day group (two mesalamine delayed-release 400 mg tablets three times a day).

Patients characteristically had a history of previous use of oral 5-ASAs (86%), steroids (41%), and rectal therapies (49%), and demonstrated clinical symptoms of three or more stools over normal per day (87%) and obvious blood in the stool most or all of the time (70%). The study population was primarily Caucasian (97%), had a mean age of 43 years (8% aged 65 years or older), and included slightly more males (56%) than females (44%).

The primary endpoint was treatment success defined as improvement from baseline to Week 6 based on the PGA. Treatment success rates were similar in the two groups: 70% in the mesalamine delayed-release group and 66% in the mesalamine delayed-release 400 mg group (difference: 5%; 95% CI: [-1.9%, 11.2%]).

A second controlled study supported the efficacy of mesalamine delayed-release at 4.8 grams per day. Treatment success was 72% in patients with moderately active UC treated with mesalamine delayed-release.

16 HOW SUPPLIED/STORAGE AND HANDLING

Mesalamine delayed-release tablets, USP are available as reddish brown, film-coated, modified capsule-shaped tablets containing 800 mg mesalamine, USP and imprinted with “TV M80” in white ink on one side and plain on the other side.

NDC 42291-489-18 Bottle of 180 tablets

Protect from moisture. Tablets can be dispensed without desiccant for up to 6 weeks.

Store at controlled room temperature, 20° to 25°C (68° to 77°F); excursions are permitted between 15° to 30°C (59° to 86°F) [see USP Controlled Room Temperature].

17 PATIENT COUNSELING INFORMATION

Administration [see Dosage and Administration (2.1)]

- Inform patients that if they are switching from a previous oral mesalamine therapy to mesalamine delayed-release tablets to discontinue their previous oral mesalamine therapy and follow the dosing instructions for mesalamine delayed-release tablets. One mesalamine delayed-release 800 mg tablet is not substitutable for two mesalamine delayed-release 400 mg oral products.
- Inform patients to take mesalamine delayed-release tablets on an empty stomach, at least 1 hour before and 2 hours after a meal.
- Instruct patients to swallow the mesalamine delayed-release tablets whole, taking care not to break, cut, or chew the tablets, because the coating is an important part of the delayed-release formulation.
- Drink an adequate amount of fluids .
- Inform patients that intact, partially intact, and/or tablet shells have been reported in the stool. Instruct patients to contact their healthcare provider if this occurs repeatedly.
- Instruct patients to protect mesalamine delayed-release tablets from moisture.

Renal Impairment

- Inform patients that mesalamine delayed-release tablets may decrease their renal function, especially if they have known renal impairment or are taking nephrotoxic drugs, including NSAIDS, and periodic monitoring of renal function will be performed while they are on therapy. Advise patients to complete all blood tests ordered by their healthcare provider [see Warnings and Precautions (5.1), Drug Interactions (7.1)] .

Mesalamine-Induced Acute Intolerance Syndrome and Other Hypersensitivity Reactions

- Inform patients of the signs and symptoms of hypersensitivity reactions. Instruct patients to stop taking mesalamine delayed-release tablets and report to their healthcare provider if they experience new or worsening symptoms of Acute Intolerance Syndrome (cramping, abdominal pain, bloody diarrhea, fever, headache, malaise, conjunctivitis and rash) or other symptoms suggestive of mesalamine-induced hypersensitivity [see Warnings and Precautions (5.2, 5.3)] .

Hepatic Failure

- Inform patients with known liver disease of the signs and symptoms of worsening liver function and advise them to report to their healthcare provider if they experience such signs or symptoms [see Warnings and Precautions (5.4)] .

Severe Cutaneous Adverse Reactions

- Inform patients of the signs and symptoms of severe cutaneous adverse reactions. Instruct patients to stop taking mesalamine delayed-release tablets and report to their healthcare provider at first appearance of a severe cutaneous adverse reaction or other sign of hypersensitivity [see Warnings and Precautions (5.5)] .

Photosensitivity

- Advise patients with pre-existing skin conditions to avoid sun exposure, wear protective clothing, and use a broad-spectrum sunscreen when outdoors [see Warnings and Precautions (5.6)] .

Nephrolithiasis

- Instruct patients to maintain an adequate fluid intake in order to minimize the risk of kidney stone formation and to contact their healthcare provider if they experience signs or symptoms of a kidney stone (e.g., severe side or back pain, blood in the urine) [see Warnings and Precautions (5.7)] .

Iron Content of Mesalamine Delayed-Release Tablets

- Advise patients to inform their healthcare provider if they take iron-containing supplements [see Warnings and Precautions (5.8)] .

Blood Disorders

- Inform elderly patients and those taking azathioprine or 6-mercaptopurine of the risk for blood disorders and the need for periodic monitoring of complete blood cell counts and platelet counts while on therapy. Advise patients to complete all blood tests ordered by their healthcare provider [see Drug Interactions (7.2), Use in Specific Populations (8.5)] .

Urine Discoloration

- Advise patients that urine may become discolored reddish-brown while taking Mesalamine Delayed-Release Tablets when it comes in contact with surfaces or water treated with hypochlorite-containing bleach. If discolored urine is observed, advise patients to observe their urine flow. Report to the healthcare provider only if urine is discolored on leaving the body, before contact with any surface or water (e.g., in the toilet)

Manufactured for:

AvKARE

Pulaski, TN 38478
Mfg. Iss. 6/24

AV 06/24 (A)